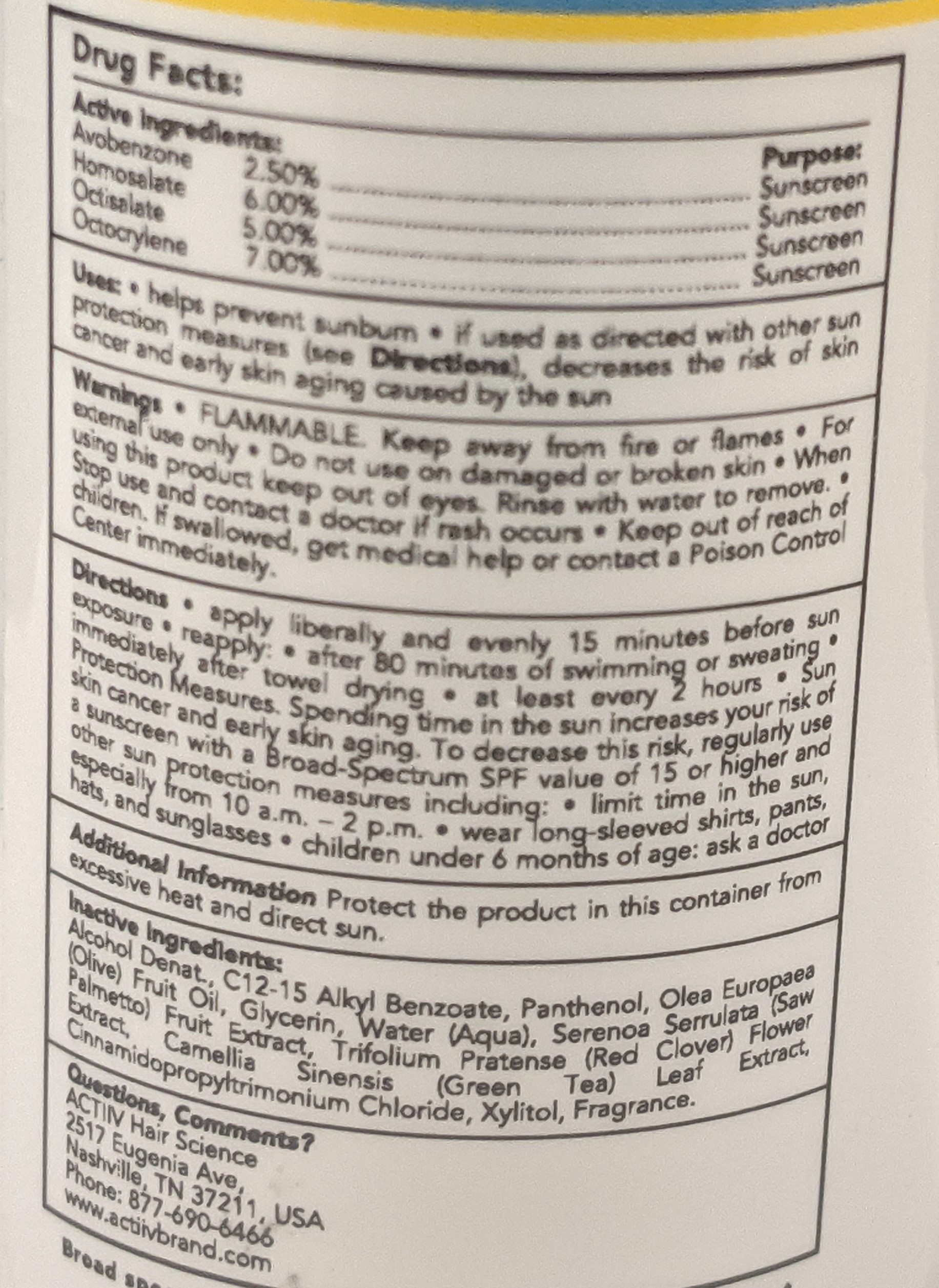 DRUG LABEL: ScalpProtectionSpray
NDC: 72496-1037 | Form: SPRAY
Manufacturer: Naturich Labs
Category: otc | Type: HUMAN OTC DRUG LABEL
Date: 20251230

ACTIVE INGREDIENTS: HOMOSALATE 6 g/100 g; OCTISALATE 5 g/100 g; AVOBENZONE 2.5 g/100 g; OCTOCRYLENE 7 g/100 g
INACTIVE INGREDIENTS: ALCOHOL 75 g/100 g

Zenagen ACTIIV Scalp Protection Spray SPF 30

Active Ingredients

Avobenzone: 2.50%

Homosalate: 6.00%

Octisalate: 5.00%

Octocrylene: 7.00%

Purpose

Sunscreen

Uses

- Helps prevent Sunburn
- if used as directed with other sun protection measures
- decreases the risk of skin cancer and early skin aging caused by the sun

Warnings

- FLAMMABLE Keep away from fire or flames
- For external use only
- Do not use on damaged or broken skin
- When using this product, keep out of eyes. Rinse with water to remove.
- Stop use and contact a doctor if rash occurs.
- Keep out of reach of children. If swallowed, get medical help or contact a Poison Control Center immediately.

Directions:

- apply liberally and evenly 15 minutes before sun exposure
- reapply: After 80 minutes of swimming or sweating, immediately after towel drying, at least every 2 hours.
- Sun Protection Measures: Spending time in the sun increases your risk of skin cancer and early skin aging. To decrease this risk, regularly use a sunscreen with a Broad-Spectrum SPF value of 15 or higher and other sun protection measures including: Limit time in the sun, especially from 10:00 a.m. - 2:00 p.m.; Wear long-sleeved shirts, pants, hats, and sunglasses; children under 6 months of age - ask a doctor.

Additional Information

Protect the product in this container from excessive heat and direct sunlight.

Inactive Ingredients:

Alcohol Denat., C12-15 Alkyl Benzoate, Panthenol, Olea Europaea (Olive) Fruit Oil, Glycerin, Water (Aqua), Serenoa Serrulata (Saw Palmetto) Fruit Extract, Trifolium Pratense (Red Clover) Flower Extract, Camellia Sinensis (Green Tea) Leaf Extract, Cinnamidopropyltrimonium Chloride, Xylitol, Fragrance.

Questions or Comments

Questions, Comments?

ACTIIV Hair Science

2517 Eugenla Ave,

Nashville, TX 37211, USA

Phone: 877-690-6466

www.actiivbrand.com

Dosage & Administration

- Apply liberally to areas exposed to sun.